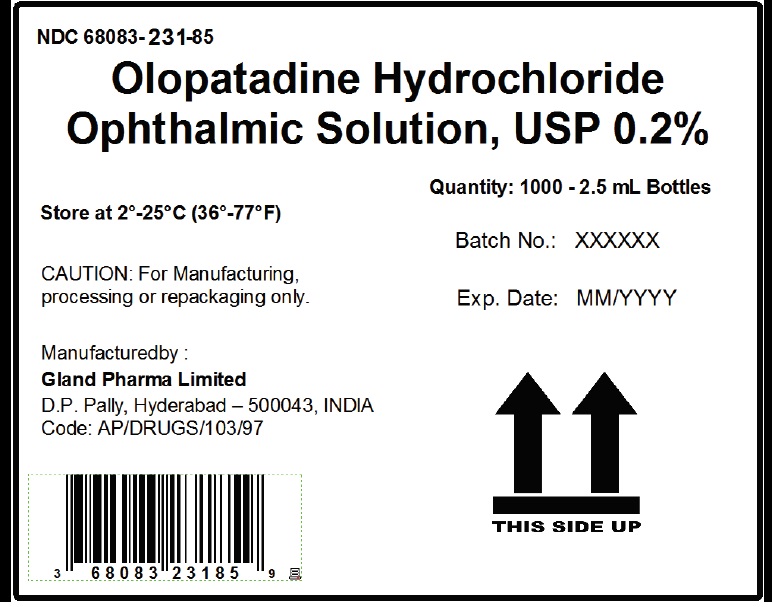 DRUG LABEL: Olopatadine Hydrochloride Ophthalmic Solution
NDC: 68083-231 | Form: SOLUTION
Manufacturer: Gland Pharma Limited
Category: other | Type: Bulk Ingredient
Date: 20221110

ACTIVE INGREDIENTS: OLOPATADINE HYDROCHLORIDE 2 mg/1 mL
INACTIVE INGREDIENTS: BENZALKONIUM CHLORIDE; SODIUM PHOSPHATE, DIBASIC, ANHYDROUS; EDETATE DISODIUM; HYDROCHLORIC ACID; POVIDONE K30; SODIUM CHLORIDE; SODIUM HYDROXIDE; WATER

PACKAGE LABEL.PRINCIPAL DISPLAY PANEL

BULK LABEL

NDC 68083-231-85

Olopatadine Hydrochloride Ophthalmic Solution, USP, 0.2%
Quantity- 1000 - 2.5 mL Bottles

Batch No. :

Mfg. Date :

Repack

Before :

Expiration Date : MM/YYYY

Store at 2°-25°C (36°-77°F)

CAUTION: For Manufacturing, processing or repackaging only.

Manufactured by :

Gland Pharma Limited

D.P. Pally, Hyderabad - 500043, INDIA

Code: AP/DRUGS/103/97